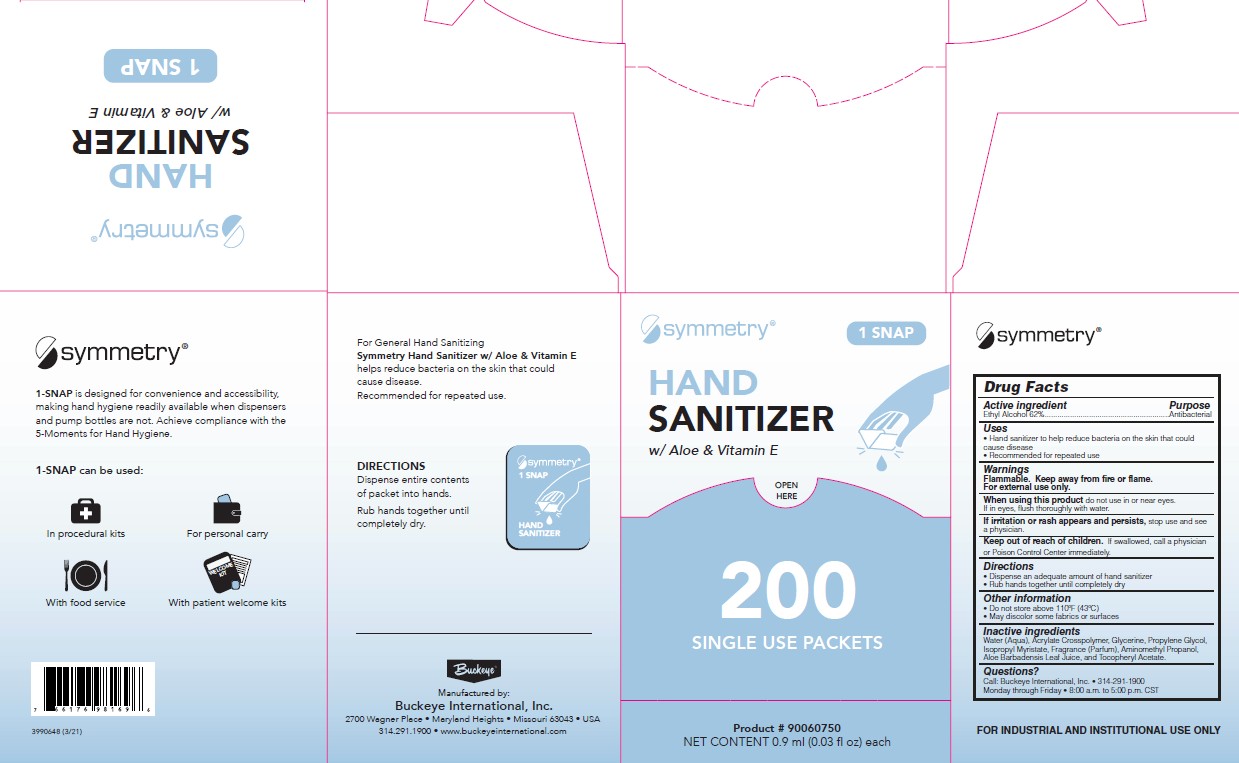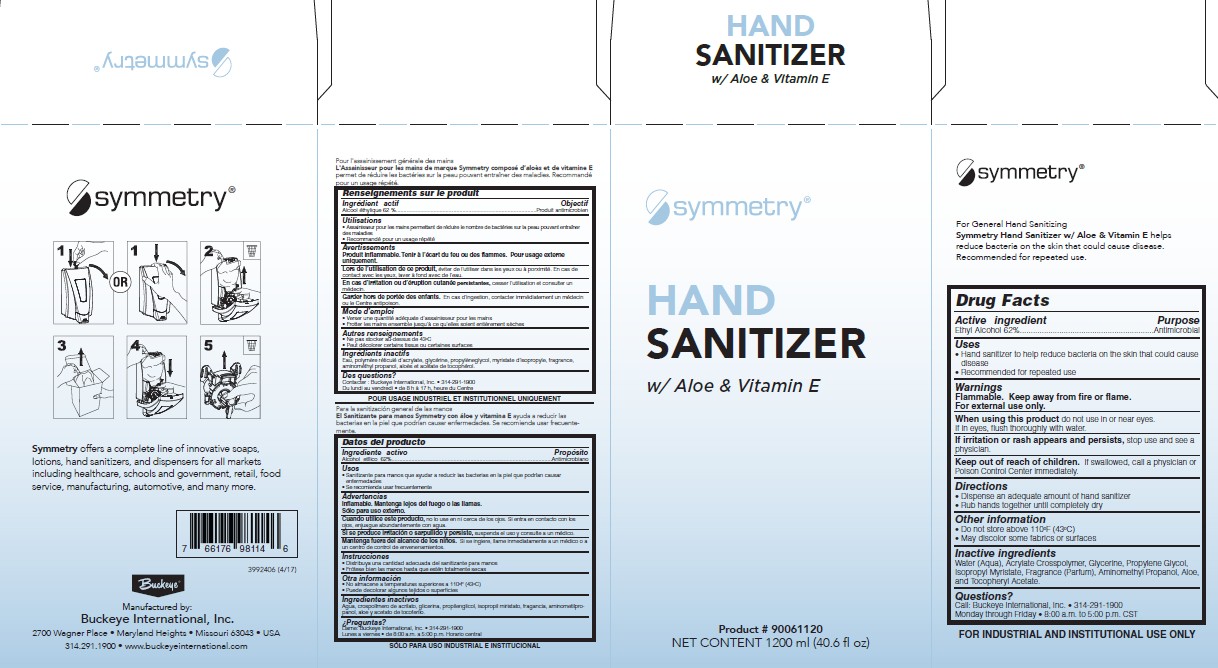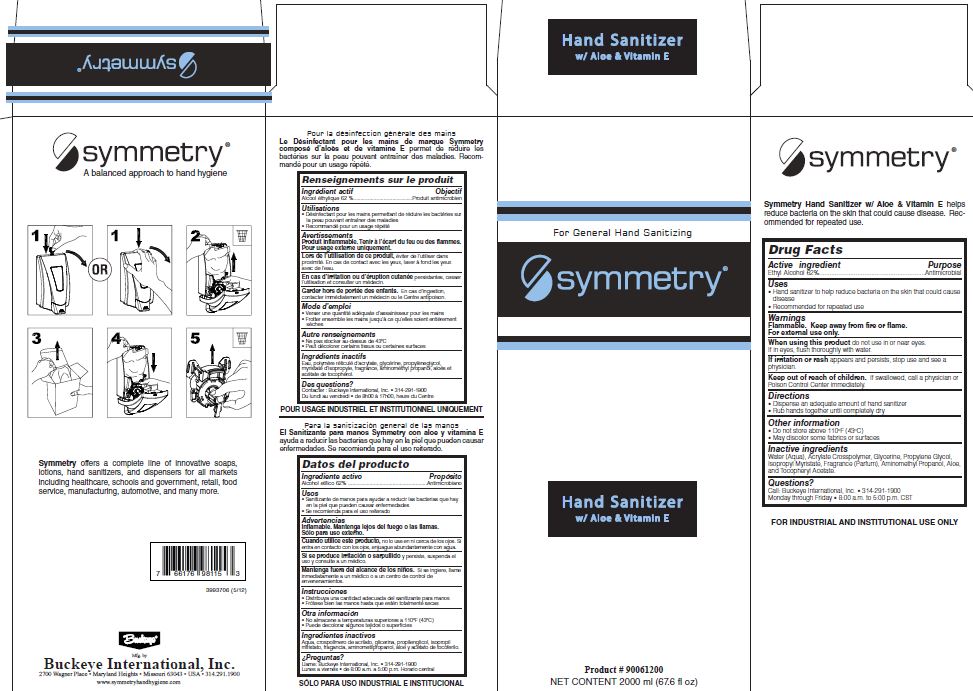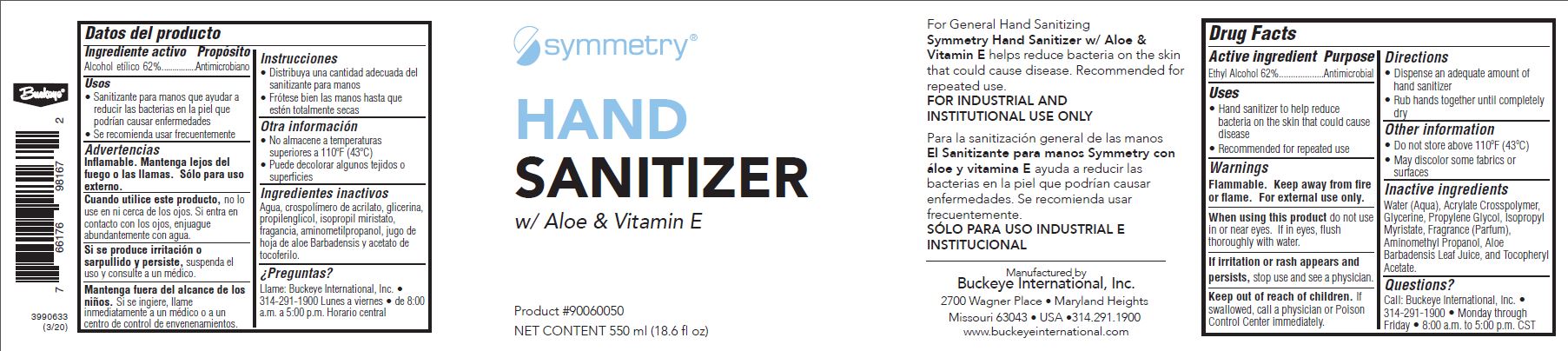 DRUG LABEL: Symmetry Hand Sanitizer
NDC: 30805-001 | Form: LIQUID
Manufacturer: Buckeye International, Inc.
Category: otc | Type: HUMAN OTC DRUG LABEL
Date: 20251029

ACTIVE INGREDIENTS: ALCOHOL 62 mL/100 mL
INACTIVE INGREDIENTS: WATER; GLYCERIN; PROPYLENE GLYCOL; ISOPROPYL MYRISTATE; AMINOMETHYLPROPANOL; ALOE; .ALPHA.-TOCOPHEROL ACETATE; CARBOMER INTERPOLYMER TYPE A (ALLYL SUCROSE CROSSLINKED)

Drug Facts 30805-001

Active ingredient

Ethyl Alcohol 62%

Uses

Hand sanitizer to help reduce bacteria on the skin that could cause disease

Recommended for repeated use

Warnings

Flammable. Keep away from fire or flame.

For external use only.

When using this product do not use in or near eyes.

If in eyes, flush thoroughly with water.

ADVERSE REACTIONS

If irritation or rash appears and persists, stop use and see a physician.

Keep out of reach of children.

If swallowed, call a physician or Poison Control Center immediately.

Directions

Dispense an adequate amount of hand sanitizer

Rub hands together until completely dry.

Other information

Do not store above 110 F (43 C)

May discolor some fabrics or surfaces

Inactive ingredients

Water (Aqua), Acrylate Crosspolymer, Glycerin, Propylene Glycol, Isopropyl Myristate, Fragrance (Parfum), Aminomethyl Propanol, Aloe, and Tocopheryl Acetate.

Questions?

Call: Buckeye International, Inc.

314-291-1900 Monday through Friday

8:00 a.m. to 5:00 p.m. CST

Purpose

Antimicrobial

PACKAGE LABEL

For General Hand Sanitizing

Symmetry

Hand Sanitizer

with Aloe and Vitamin E

Symmetry Hand Sanitizer with Aloe and Vitamin E helps reduce bacteria on the skin that could cause disease.

Recommended for repeated use.

Product 90061200

Net Contents 2000 ml (67.6 fl oz)